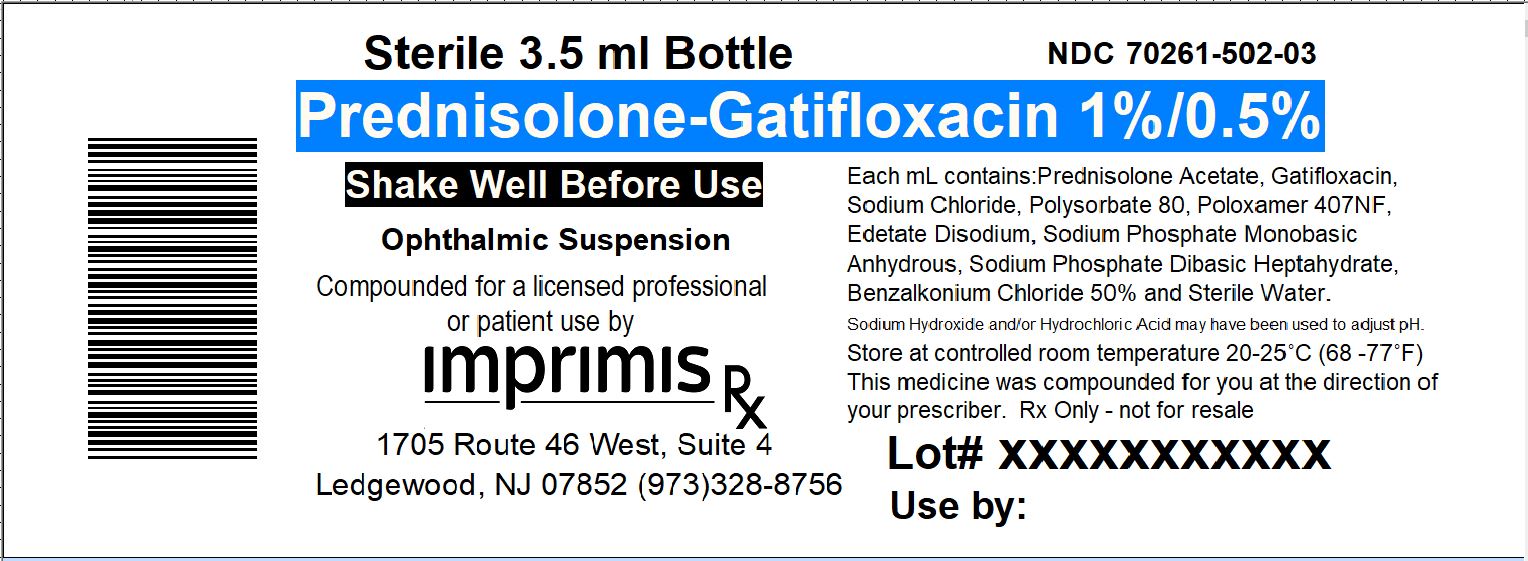 DRUG LABEL: Pred-Gati
NDC: 70261-502 | Form: SUSPENSION
Manufacturer: ImprimisRx NJ
Category: prescription | Type: HUMAN PRESCRIPTION DRUG LABEL
Date: 20180222

ACTIVE INGREDIENTS: PREDNISOLONE ACETATE 10 mg/1 mL; GATIFLOXACIN HEMIHYDRATE 5 mg/1 mL
INACTIVE INGREDIENTS: SODIUM PHOSPHATE, DIBASIC, HEPTAHYDRATE 1.9 mg/1 mL

STORAGE AND HANDLING

Store at 20° to 25° C (68° to 77° F)